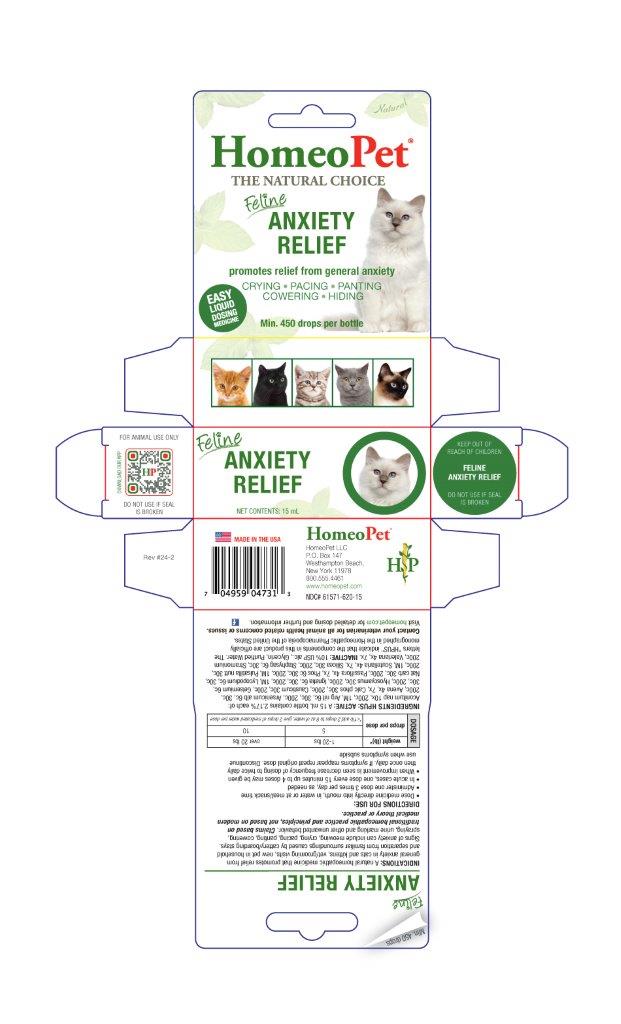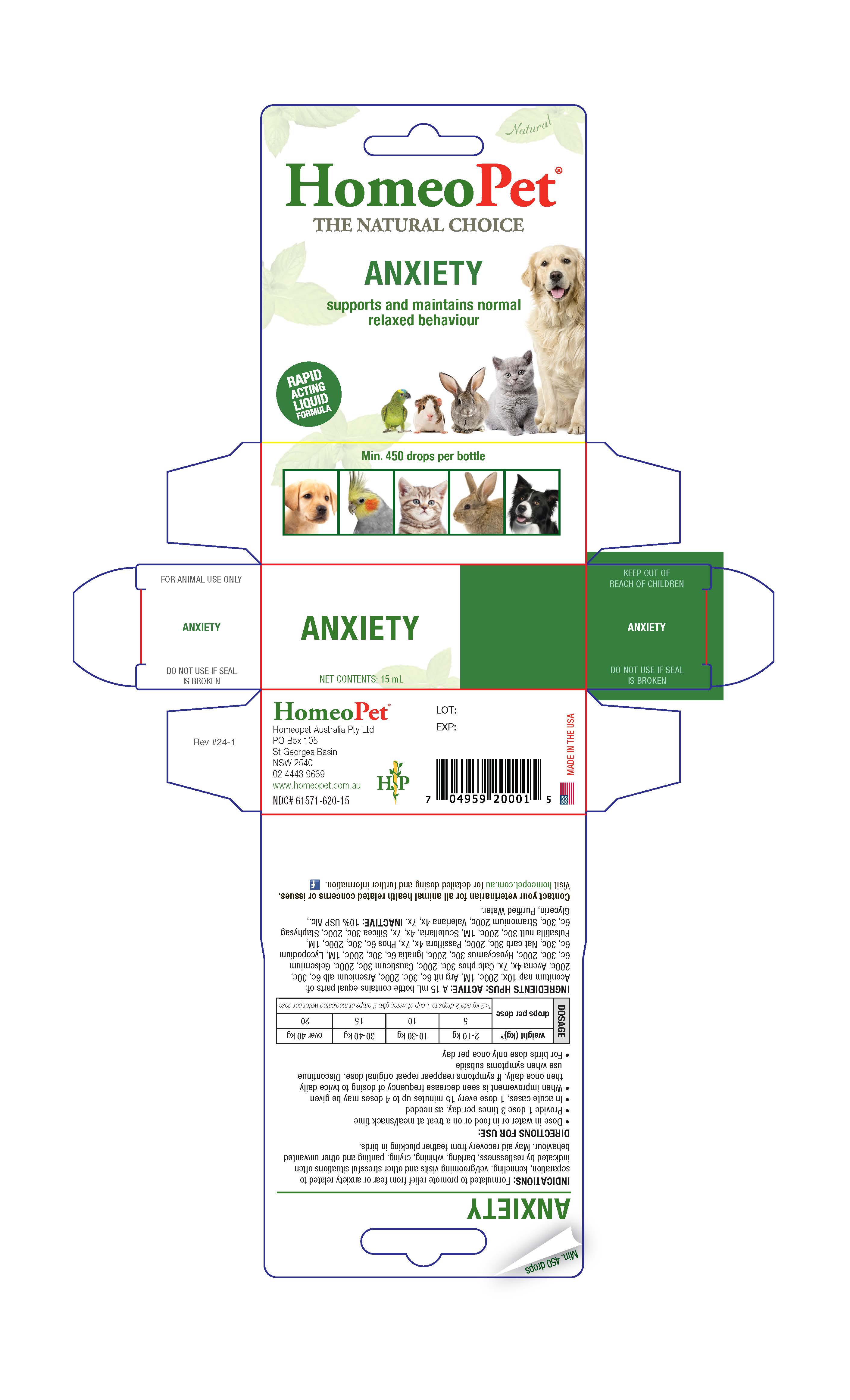 DRUG LABEL: Anxiety Relief
NDC: 61571-620 | Form: LIQUID
Manufacturer: HomeoPet, LLC
Category: homeopathic | Type: OTC ANIMAL DRUG LABEL
Date: 20251216

ACTIVE INGREDIENTS: ACONITUM NAPELLUS 10 [hp_X]/15 mL; SILVER NITRATE 6 [hp_C]/15 mL; ARSENIC TRIOXIDE 6 [hp_C]/15 mL; AVENA SATIVA FLOWERING TOP 4 [hp_X]/15 mL; TRIBASIC CALCIUM PHOSPHATE 30 [hp_C]/15 mL; CAUSTICUM 30 [hp_C]/15 mL; GELSEMIUM SEMPERVIRENS ROOT 6 [hp_C]/15 mL; HYOSCYAMUS NIGER 6 [hp_C]/15 mL; STRYCHNOS IGNATII SEED 6 [hp_C]/15 mL; LYCOPODIUM CLAVATUM SPORE 6 [hp_C]/15 mL; SODIUM CARBONATE 30 [hp_C]/15 mL; PASSIFLORA INCARNATA TOP 4 [hp_X]/15 mL; PHOSPHORUS 6 [hp_C]/15 mL; PULSATILLA PATENS 30 [hp_C]/15 mL; SCUTELLARIA LATERIFLORA 4 [hp_X]/15 mL; SILICON DIOXIDE 30 [hp_C]/15 mL; DELPHINIUM STAPHISAGRIA SEED 6 [hp_C]/15 mL; DATURA STRAMONIUM 200 [hp_C]/15 mL; VALERIAN  4 [hp_X]/15 mL
INACTIVE INGREDIENTS: ALCOHOL; WATER; GLYCERIN

Feline Anxiety Relief

Feline Anxiety Relief

Promotes relief from general anxiety

CRYING-PACING-PANTING

COWERING-HIDING

Directions for Use and Dosage

- Dose remedy directly into mouth, in water or at meal/snack time
- Administer one dose 3 times per day, as needed
- In acute cases, one dose every 15 minutes up to 4 doses may be given
- When improvement is seen decrease frequency of dosing to twice daily, then once daily. If symptoms reappear repeat original dose. Discontinue use when symptoms subside

weight (lb) | drops per dose
kittens less than 1 lb | 2 in at least 8 oz of water
1-20 | 5
over 20 | 10

Contact Veterinarian

Contact your veterinarian for all animal health related concerns or issues.

Visit homeopet.com for detailed dosing and further information.

Ingredients HPUS: Active

Aconitum nap 10x, 200c, 1M, Arg nit 6c, 30c, 200c, Arsenicum alb 6c, 30c, 200c, Avena 4x, 7x, Cal phos 30c, 200c, Causticum 30c, 200c, Gelsemium 6c, 30c, 200c, Hyoscyamus 30c, 200c, Ignatia 6c, 30c, 200c, 1M, Lycopodium 6c, 30c, Nat carb 30c, 200c, Passiflora 4x, 7x, Phos 6c, 30c, 200c, 1M, Pulsatilla nutt 30c, 200c, 1M, Scutellaria 4x, 7x, Silicea 30c, 200c, Staphysag 6c, 30c, Stramonium 200c, Valeriana 4x, 7x

Inactive Ingredients

USP Alcohol, Glycerin, Purified Water

Indications

A homeopathic medicine that promotes relief from general anxiety in cats and kittens, vet/grooming visits, new pet in household and separation from familiar surroundings caused by cattery/boarding stays. Signs of anxiety can include meowing, crying, pacing, panting, cowering, spraying, urine marking and other unwanted behavior. Claims based on traditional homeopathic practice and principles, not based on modern medical theory or practice.